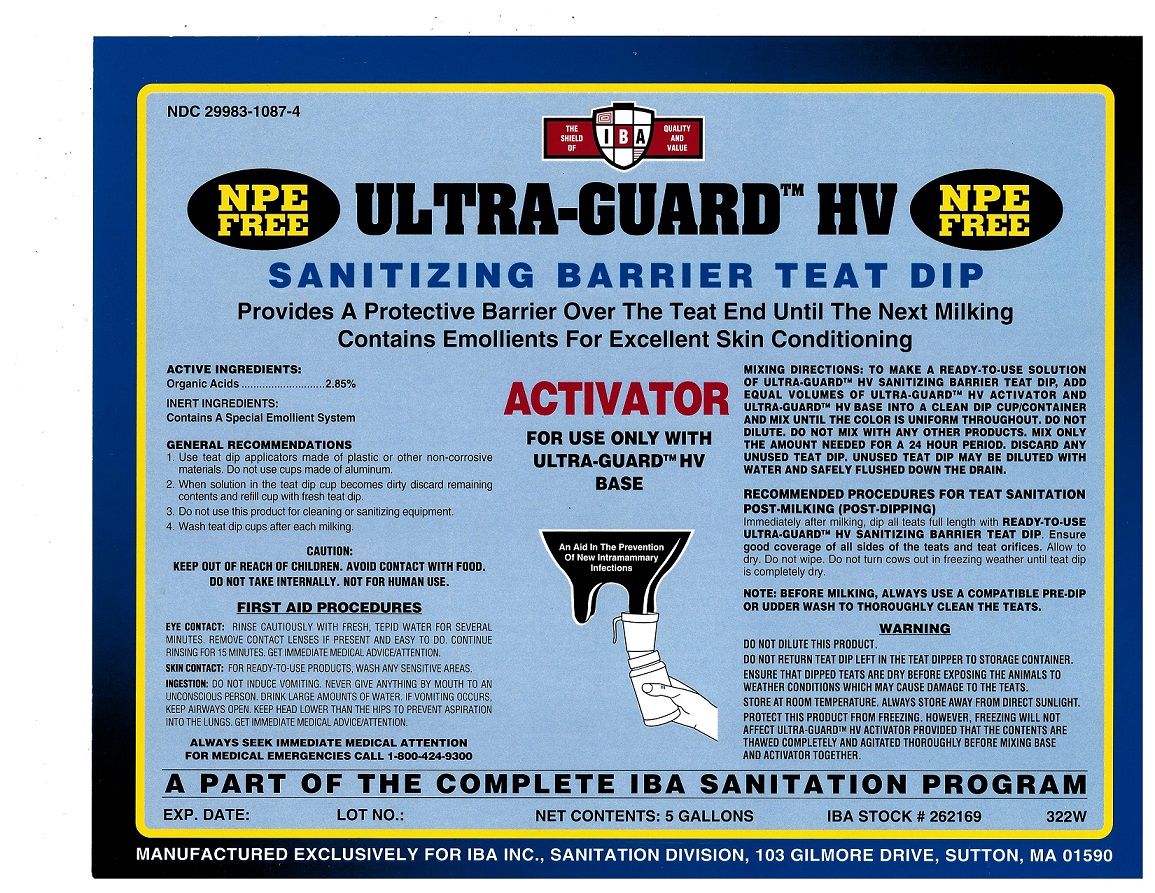 DRUG LABEL: Ultra-Guard HV Activator
NDC: 29983-1087 | Form: LIQUID
Manufacturer: IBA
Category: animal | Type: OTC ANIMAL DRUG LABEL
Date: 20251211

ACTIVE INGREDIENTS: LACTIC ACID 2.85 kg/100 kg

Ultra-Guard HV Activator

Active Ingredient

Organic Acids 2.85%

Inert Ingredients

Contains special emollient system

Mixing Directions

To make a ready-to-use solution of Ultra-Guard HV Sanitizing Barrier Teat Dip, add equal volumes of Ultra-Guard HV Activator and Ultra-Guard HV Base into a clean dip cup/container and mix until the color is uniform throughout. Do not dilute. Do not mix with any other products. Mix only the amount needed for a 24 hour period. Discard any unused teat dip. Unused teat dip may be diluted with water and safely flushed down the drain.

Recommended Procedures for Teat Sanitation

POST-MILKING (POST-DIPPING)

Immediately after milking, dip all teats full length with RTU Ultra-Guard HV Sanitizing Barrier Teat Dip. Ensure good coverage of all sides of the teats and teat orifices. Allow to dry. Do not wipe. Do not turn cows out in freezing weather until teat dip is completely dry.

Note: Before milking, always use a compatible pre-dip or udder wash to thoroughly clean the teats.

Caution

Keep out of reach of children. Avoid contact with food. Do not take internally. Not for human use.

First Aid

EYE CONTACT: Rinse cautiously with fresh, tepid water for several minutes. Remove contact lenses if present and easy to do. Continue rinsing for 15 minutes. Get immediate medical advice/attention. SKIN CONTACT: For RTU products wash any sensitive areas. INGESTION: Do not induce vomitting. Never give anything by mouth to an unconscious person. Drink large amounts of water. If vomitting occurs, keep airways open. Keep head lower than the hipsto prevent aspiration into the lungs. Get immediate medical advice/attention.

Warning

Do not dilute this product.
Do not return teat dip left in the teat dipper to storage container.
Ensure that dipped teats are dry before exposing the animals to weather conditions which may cause damage to the teats.
Store at room temperature. Always store away from direct sunlight.
Protect this product from freezing. However, freezing will not affect Ultra-Guard HV Activator provided that the contents are thawed completely and agitated thoroughly before mixing base and activator together.